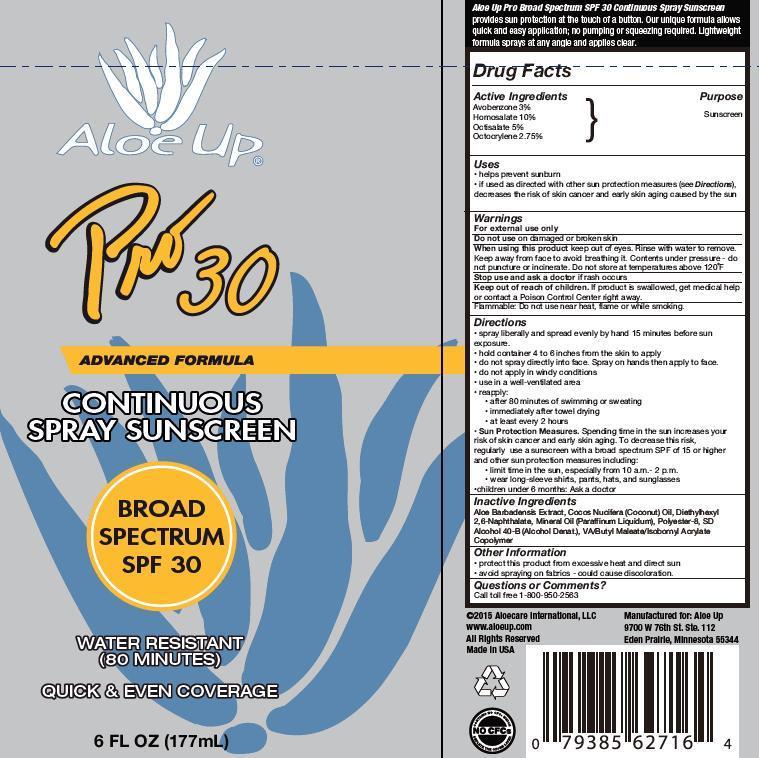 DRUG LABEL: ALOE UP
NDC: 13630-0095 | Form: SPRAY
Manufacturer: Prime Packaging Inc.
Category: otc | Type: HUMAN OTC DRUG LABEL
Date: 20150922

ACTIVE INGREDIENTS: AVOBENZONE 24.9 mg/1 mL; HOMOSALATE 83 mg/1 mL; OCTISALATE 41.5 mg/1 mL; OCTOCRYLENE 22.8 mg/1 mL
INACTIVE INGREDIENTS: ALCOHOL; DIETHYLHEXYL 2,6-NAPHTHALATE; MINERAL OIL; COCONUT OIL; ALOE VERA LEAF; POLYESTER-8 (1400 MW, CYANODIPHENYLPROPENOYL CAPPED); DIBUTYL MALEATE

ALOE UP BROAD SPECTRUM SPF 50

Active Ingredients

Avobenzone 3%

Homosalate 10%

Octisalate 5%

Octocrylene 2.75%

PURPOSE

Sunscreen

Uses

- helps prevent sunburn
- if used as directed with other sun protection measures (see Directions), decreases the risk of skin cancer and early skin aging caused by the sun

WARNINGS

For external use only.

Do not use on damaged or broken skin

When using this product keep out of eyes. Rinse with water to remove. Keep away from face to avoid breathing it. Contents under pressure - not puncture or incinerate. Do not store at temperatures above 120°F

Flammable: Do not use near heat, flame or while smoking.

Directions

- spray liberally and spread evenly by hand 15 minutes before sun exposure
- hold container 4 to 6 inches from the skin to apply
- do not spray directly into face. Spray on hands then apply to face.
- do not apply in windy conditions
- use in a well ventilated area
- reapply:
- after 80 minutes of swimming or sweating
- immediately after towel drying
- at least every 2 hours
- Sun Protection Measures. Spending time in the sun increases your risk of skin cancer and early skin aging. To decrease this risk, regularly use a sunscreen with broad spectrum SPF of 15 or higher and other sun protection measures including:
- limit time in the sun, especially from 10 a.m. – 2 p.m.
- wear long-sleeve shirts, pants, hats, and sunglasses
- children under 6 months: Ask a doctor

INACTIVE INGREDIENT

Aloe Barbadensis Extract, Cocos Nucifera (Coconut) Oil, Diethylhexyl 2,6-Napthalate, Mineral Oil (Paraffinum Liquidum), Polyester-8, SD Alcohol 40-B (Alcohol Denat.), VA/Butyl Maleate/Isobornyl Acrylate Copolymer

Other Information

- protect this product from excesive heat and direct sun
- avoid spraying on fabrics - could cause discoloration

Questions or Comments?

Call toll free 1-800-950-2563